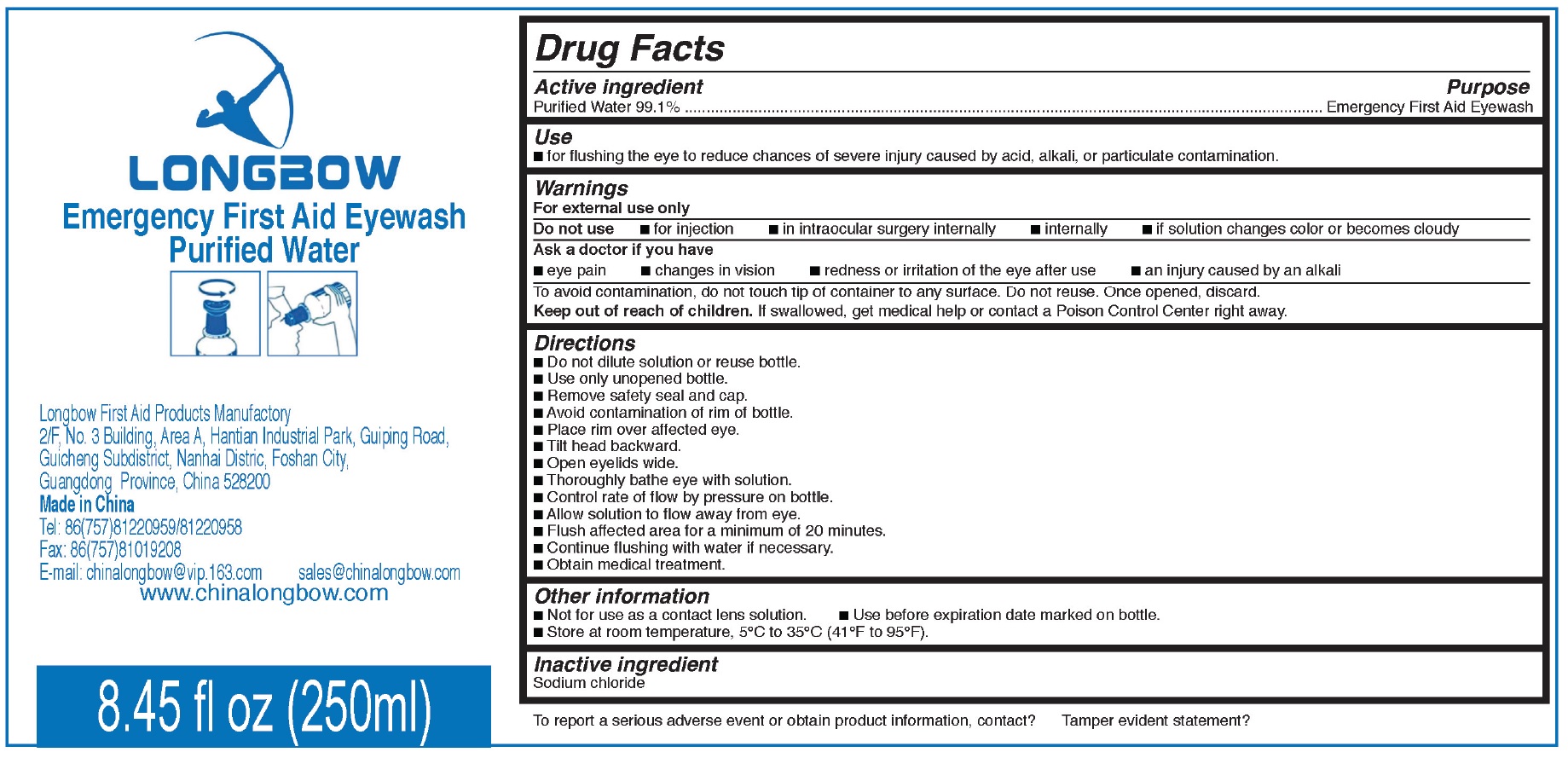 DRUG LABEL: Emergency First Aid Eyewash Purified Water
NDC: 70746-001 | Form: LIQUID
Manufacturer: Longbow First Aid Products Manufactory
Category: otc | Type: HUMAN OTC DRUG LABEL
Date: 20161208

ACTIVE INGREDIENTS: WATER 999.1 mg/1 mL
INACTIVE INGREDIENTS: SODIUM CHLORIDE

Emergency First Aid Eyewash Purified Water

Active ingredient

Purified Water 99.1%

Purpose

Emergency First Aid Eye Wash

Use

- for flushing the eye to reduce chances of severe injury caused by acid, alkali or particulate contamination.

Warnings

For external use only.

Do not use

- for injection
- in intraocular surgery internally
- internally
- if solution changes color and become cloudy

Ask a doctor if you have

- eye pain
- changes in vision
- redness or irritation occurs of the eye after use
- an injury caused by an alkali

To avoid contamination, do not touch tip of container to any surface. Do not reuse. Once opened, discard.

Keep out of reach of children.

If swallowed, get medical help or contact a Poison Control Center right away.

Directions

- Do not dilute solution or reuse bottle.
- Use only unopened bottle.
- Remove safely seal and cap
- Avoid contamination of rim of bottle.
- Place rim over affected eye.
- Tilt head backward.
- Open eyelids wide.
- Thoroughly bathe eye with solution.
- Control rate of flow by pressure on bottle.
- Allow solution to flow away from eye.
- Flush affected area for a minumum of 20 minutes.
- Continue flushing with water if necessary.
- Obtain medical treatment.

Other information

- Not for use as a contact lens solution.
- Use before expiration date marked on the bottle.
- Store at room temperature, 5^0C to 35^0C (41^0F to 95^0F)

Inactive ingredient

Sodium chloride